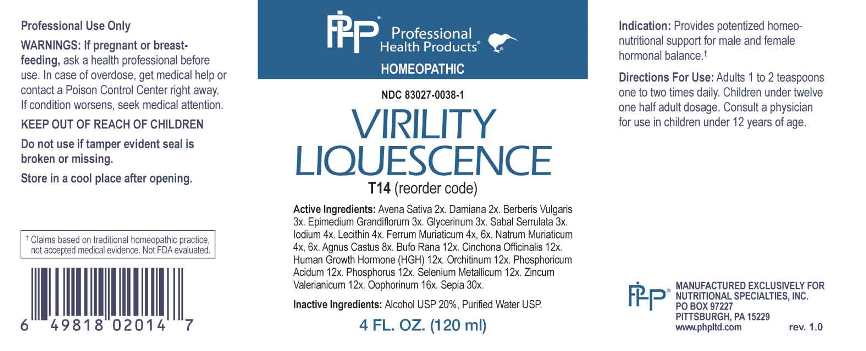 DRUG LABEL: Virility Liquescence
NDC: 83027-0038 | Form: LIQUID
Manufacturer: Nutritional Specialties, Inc.
Category: homeopathic | Type: HUMAN OTC DRUG LABEL
Date: 20230329

ACTIVE INGREDIENTS: AVENA SATIVA FLOWERING TOP 2 [hp_X]/1 mL; TURNERA DIFFUSA LEAFY TWIG 2 [hp_X]/1 mL; BERBERIS VULGARIS ROOT BARK 3 [hp_X]/1 mL; EPIMEDIUM GRANDIFLORUM TOP 3 [hp_X]/1 mL; GLYCERIN 3 [hp_X]/1 mL; SAW PALMETTO 3 [hp_X]/1 mL; IODINE 4 [hp_X]/1 mL; EGG PHOSPHOLIPIDS 4 [hp_X]/1 mL; FERRIC CHLORIDE HEXAHYDRATE 4 [hp_X]/1 mL; SODIUM CHLORIDE 4 [hp_X]/1 mL; CHASTE TREE FRUIT 8 [hp_X]/1 mL; BUFO BUFO CUTANEOUS GLAND 12 [hp_X]/1 mL; CINCHONA OFFICINALIS BARK 12 [hp_X]/1 mL; SOMATROPIN 12 [hp_X]/1 mL; BOS TAURUS TESTICLE 12 [hp_X]/1 mL; PHOSPHORIC ACID 12 [hp_X]/1 mL; PHOSPHORUS 12 [hp_X]/1 mL; SELENIUM 12 [hp_X]/1 mL; ZINC VALERATE DIHYDRATE 12 [hp_X]/1 mL; SUS SCROFA OVARY 16 [hp_X]/1 mL; SEPIA OFFICINALIS JUICE 30 [hp_X]/1 mL
INACTIVE INGREDIENTS: WATER; ALCOHOL

DRUG FACTS:

ACTIVE INGREDIENTS:

Avena Sativa 2X, Damiana 2X, Berberis Vulgaris 3X, Epimedium Grandiflorum 3X, Glycerinum 3X, Sabal Serrulata 3X, Iodium 4X, Lecithin 4X, Ferrum Muriaticum 4X, 6X, Natrum Muriaticum 4X, 6X, Agnus Castus 8X, Bufo Rana 12X, Cinchona Officinalis 12X, Human Growth Hormone (HGH) 12X, Orchitinum 12X, Phosphoricum Acidum 12X, Phosphorus 12X, Selenium Metallicum 12X, Zincum Valerianicum 12X, Oophorinum 16X, Sepia 30X.

PURPOSE:

Provides potentized homeo-nutritional support for male and female hormonal balance.†

†Claims based on traditional homeopathic practice, not accepted medical evidence. Not FDA evaluated.

WARNINGS:

Professional Use Only

If pregnant or breast-feeding, ask a health professional before use.

In case of overdose, get medical help or contact a Poison Control Center right away.

If condition worsens, seek medical attention.

KEEP OUT OF REACH OF CHILDREN

Do not use if tamper evident seal is broken or missing.

Store in a cool place after opening

KEEP OUT OF REACH OF CHILDREN:

In case of overdose, get medical help or contact a Poison Control Center right away.

DIRECTIONS:

Adults 1 to 2 teaspoons one to two times daily. Children under twelve one half adult dosage. Consult a physician for use in children under 12 years of age.

INDICATIONS:

Provides potentized homeo-nutritional support for male and female hormonal balance.†

†Claims based on traditional homeopathic practice, not accepted medical evidence. Not FDA evaluated.

INACTIVE INGREDIENTS:

Alcohol USP 20%, Purified Water USP.

QUESTIONS:

MANUFACTURED EXCLUSIVELY FOR

NUTRITIONAL SPECIALTIES, INC.

PO BOX 97227

PITTSBURG, PA 15229

www.phpltd.com

PACKAGE LABEL DISPLAY:

Professional

Health Products

HOMEOPATHIC

NDC 83027-0038-1

VIRILITY

LIQUESCENCE

4 FL. OZ (120 ml)